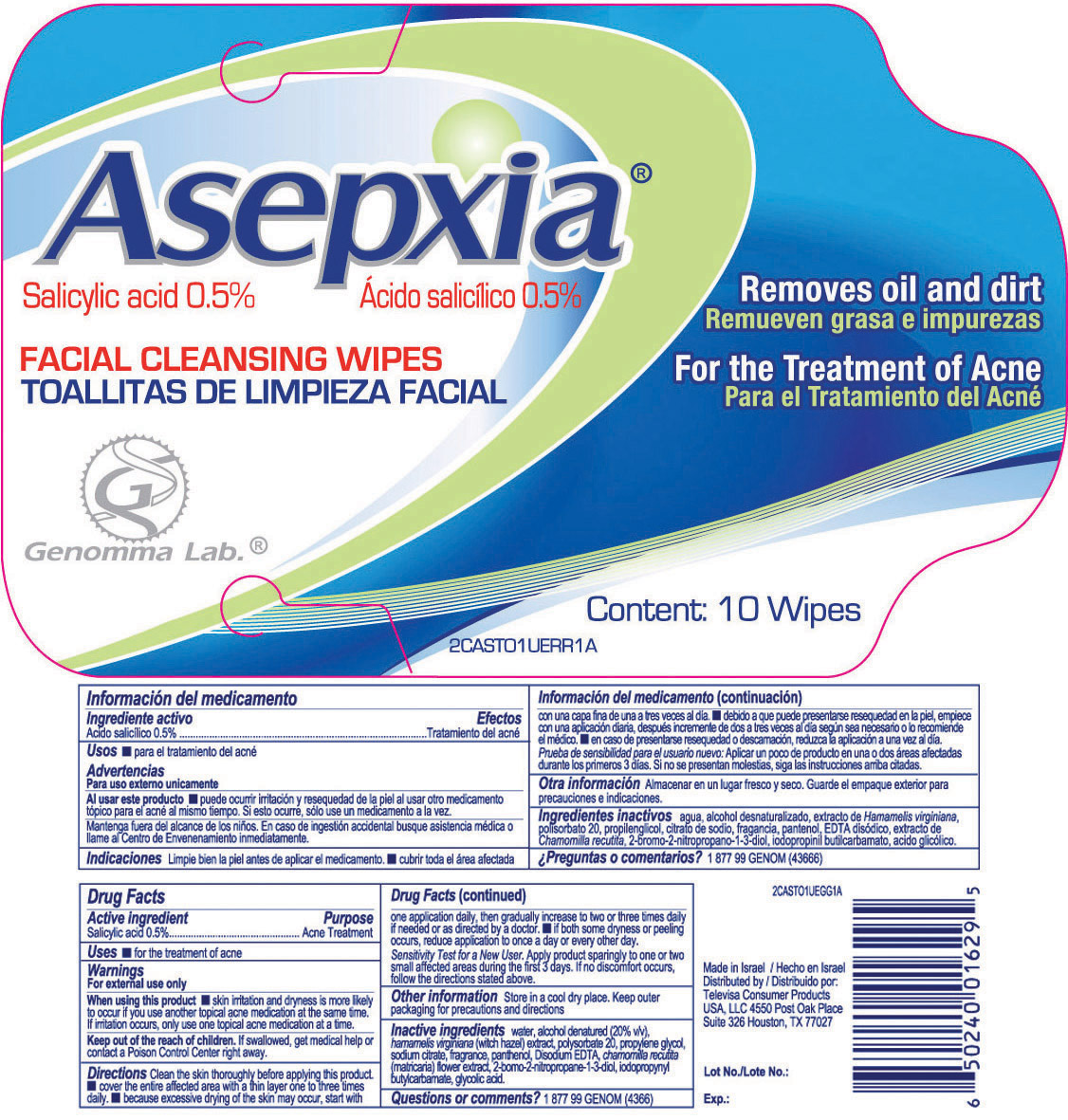 DRUG LABEL: Asepxia
NDC: 59886-410 | Form: CLOTH
Manufacturer: Fischer Pharmaceuticals Ltd.
Category: otc | Type: HUMAN OTC DRUG LABEL
Date: 20110111

ACTIVE INGREDIENTS: SALICYLIC ACID   0.5 g/100 g
INACTIVE INGREDIENTS: WATER; ALCOHOL; HAMAMELIS VIRGINIANA LEAF; POLYSORBATE 20; PROPYLENE GLYCOL          ; SODIUM CITRATE; PANTHENOL; EDETATE DISODIUM; CHAMOMILE; BRONOPOL; IODOPROPYNYL BUTYLCARBAMATE; GLYCOLIC ACID

Asepxia

Drug Facts

Active ingredient Purpose

Salicylic acid 0.5%................ Acne Treatment

Uses

Enter section text here

INDICATIONS AND USAGE

- for the treatment of acne

Warnings

For external use only

When using this product

skin irritation and dryness is more likely to occur if you use another topical acne medication at the same time.

If irritation occurs, only use one topical acne medication at a time.

Keep out of the reach of children.

If swallowed, get medical help or contact a Poison Control Center right away.

Directions

Clean the skin thoroughly before applying this product.

- cover the entire affected area with a thin layer one to three times daily.
- because excessive drying of the skin may occur, start with one application daily, then gradually increase to two or three times daily if needed or as directed by a doctor.
- if both some dryness or peeling occurs, reduce application to once a day or every other day.

Sensitivity Test for a New User. Apply product sparingly to one or two small affected areas during the first 3 days. If no discomfort occurs, follow the directions stated above.

Other information

Store in a cool dry place. Keep outer packaging for precautions and directions

Inactive ingredients

water, alcohol denatured (20% vlv), hamamelis virginiana (witch hazel) extracts, polysorobate 20, propylene glycol, sodium citrate, fragrance, panthenol, Disodium EDTA, chamomila recutita (matricaria) flower extract, 2-bomo-2-nitropropane-1-3-diol, iodopropynyl butylcarbamate, glycolic acid.

Questions or comments?

1 877 99 GENOM (4366)

PACKAGE LABEL

(front of packet)

Remove oil and dirt

For the treatment of Acne

Content: 10 Wipes

(back of packet)

Made in Israel

Distributed by

Televisa Consumer Products

USA, LLC 4550 Post Oak Place

Suite 326 Houston, TX 77027

Lot No

Exp.: